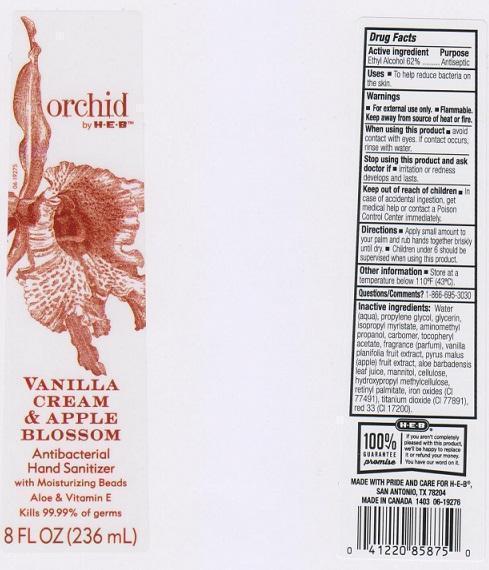 DRUG LABEL: ORCHID
NDC: 37808-165 | Form: LIQUID
Manufacturer: H E B
Category: otc | Type: HUMAN OTC DRUG LABEL
Date: 20150116

ACTIVE INGREDIENTS: ALCOHOL 620 mg/1 mL
INACTIVE INGREDIENTS: WATER; PROPYLENE GLYCOL; GLYCERIN; ISOPROPYL MYRISTATE; AMINOMETHYLPROPANOL; CARBOMER 934; .ALPHA.-TOCOPHEROL ACETATE; VANILLA; APPLE; ALOE VERA LEAF; MANNITOL; POWDERED CELLULOSE; HYPROMELLOSES; VITAMIN A PALMITATE; FERRIC OXIDE RED; TITANIUM DIOXIDE; D&C RED NO. 33

DRUG FACTS

ACTIVE INGREDIENT

ETHYL ALCOHOL 62%

PURPOSE

ANTISEPTIC

USES

TO HELP REDUCE BACTERIA ON THE SKIN

WARNINGS

FOR EXTERNAL USE ONLY

WHEN USING THIS PRODUCT

AVOID CONTACT WITH EYES. IF CONTACT OCCURS, RINSE WITH WATER

STOP USING THIS PRODUCT AND ASK DOCTOR IF

IRRITATION OR REDNESS DEVELOPS AND LASTS

KEEP OUT OF REACH OF CHILDREN

IN CASE OF ACCIDENTAL INGESTION, GET MEDICAL HELP OR CONTACT A POISON CONTROL CENTER IMMEDIATELY

DIRECTIONS

- APPLY SMALL AMOUNT TO YOUR PALM AND RUB HANDS TOGETHER BRISKLY UNTIL DRY
- CHILDREN UNDER 6 SHOULD BE SUPERVISED WHEN USING THIS PRODUCT

OTHER INFORMATION

STORE AT A TEMPERATURE BELOW 110°F (43°C)

QUESTIONS/COMMENTS?

1-866-695-3030

INACTIVE INGREDIENTS

WATER (AQUA), PROPYLENE GLYCOL, GLYCERIN, ISOPROPYL MYRISTATE, AMINOMETHYL PROPANOL, CARBOMER, TOCOPHERYL ACETATE, FRAGRANCE (PARFUM), VANILLA PLANIFOLIA FRUIT EXTRACT, PYRUS MALUS (APPLE) FRUIT EXTRACT, ALOE BARBADENSIS LEAF JUICE, MANNITOL, CELLULOSE, HYDROXYPROPYL METHYLCELLULOSE, RETINYL PALMITATE, IRON OXIDES (CI 77491), TITANIUM DIOXIDE (CI 77891), RED 33 (CI 17200)